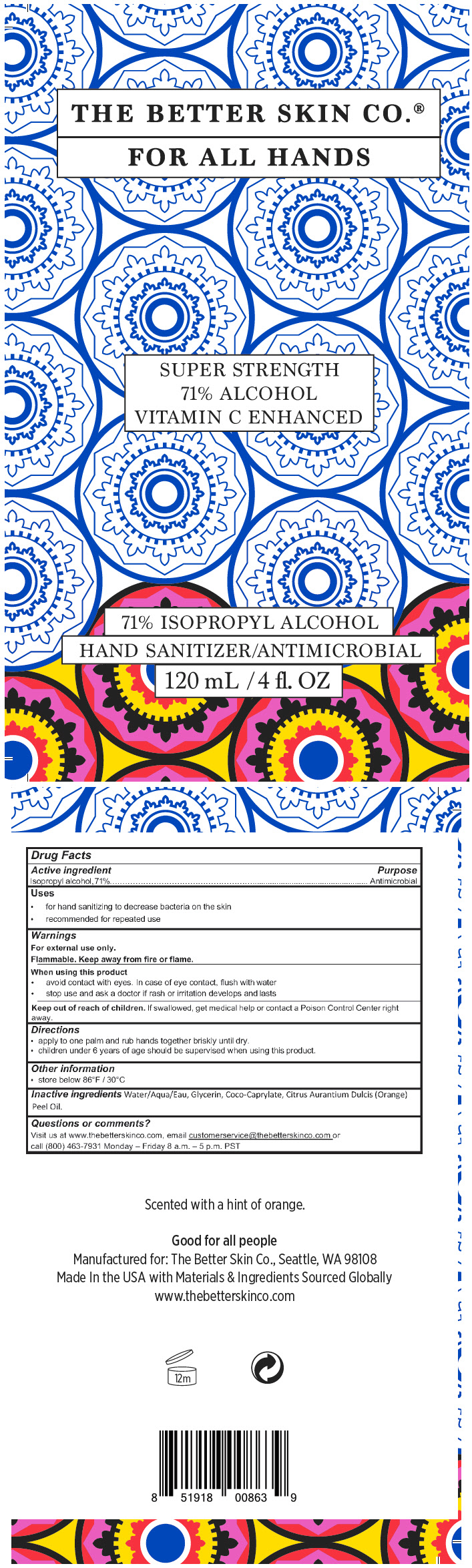 DRUG LABEL: HAND SANITIZER
NDC: 71716-102 | Form: GEL
Manufacturer: Mirakle Cosmetics LLC dbaThe Better Skin Co.
Category: otc | Type: HUMAN OTC DRUG LABEL
Date: 20200625

ACTIVE INGREDIENTS: Alcohol 71 mL/100 mL
INACTIVE INGREDIENTS: WATER; GLYCERIN; COCO-CAPRYLATE; ORANGE OIL

HAND SANITIZER

Drug Facts

Active ingredient

Isopropyl alcohol, 71%

Purpose

Antimicrobial

Uses

- for hand sanitizing to decrease bacteria on the skin
- recommended for repeated use

Warnings

For external use only.

Flammable. Keep away from fire or flame.

When using this product

- avoid contact with eyes. In case of eye contact, flush with water
- stop use and ask a doctor if rash or irritation develops and lasts

Keep out of reach of children. If swallowed, get medical help or contact a Poison Control Center right away.

Directions

- apply to one palm and rub hands together briskly until dry.
- children under 6 years of age should be supervised when using this product.

Other information

- store below 86°F / 30°C

Inactive ingredients

Water/Aqua/Eau, Glycerin, Coco-Caprylate, Citrus Aurantium Dulcis (Orange) Peel Oil.

Questions or comments?

Visit us at www.thebetterskinco.com, email customerservice@thebetterskinco.com or call (800) 463-7931 Monday – Friday 8 a.m. – 5 p.m. PST

PRINCIPAL DISPLAY PANEL - 120 mL Bottle Label

THE BETTER SKIN CO.®
FOR ALL HANDS

SUPER STRENGTH
71% ALCOHOL
VITAMIN C ENHANCED

71% ISOPROPYL ALCOHOL
HAND SANITIZER/ANTIMICROBIAL
120 mL / 4 fl. OZ